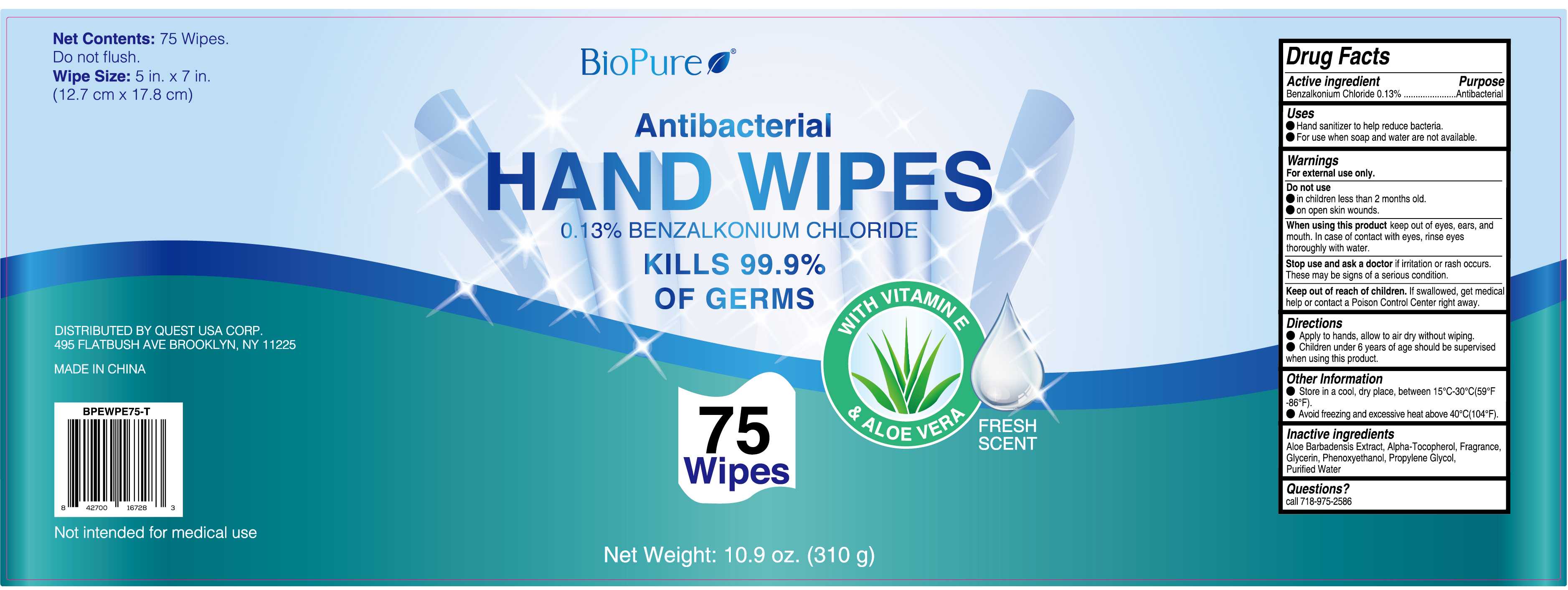 DRUG LABEL: WET WIPE
NDC: 79866-012 | Form: CLOTH
Manufacturer: Osike Cosmetics Co., Ltd.
Category: otc | Type: HUMAN OTC DRUG LABEL
Date: 20220111

ACTIVE INGREDIENTS: BENZALKONIUM CHLORIDE 0.13 1/100 1
INACTIVE INGREDIENTS: GLYCERIN; ALOE VERA LEAF; WATER; .ALPHA.-TOCOPHEROL, DL-; PHENOXYETHANOL; PROPYLENE GLYCOL

79866-012
WET WIPE

Active Ingredient(s)

Benzalkonium Chloride 0.13% ……………………………………………...Antimicroblal

Purpose

Antimicroblal

Use

●Hand sanitizer to help reduce bacteria

●For use when soap and water are not available.

Warnings

For external use only.

Do not use

●in children less than 2 months old.

●on open skin wounds

WHEN USING

keep out of eyes, ears, and mouth. In case of contact with eyes, rinse eyes thoroughly with water.

Stop use and ask a doctor if irritation or rash occurs. These may be signs of a serious condition

Keep out of reach of children. If swallowed. get medical help or contact a Poison Control Center right away.

Directions

●Apply to hands, allow to air dry without wiping.

●Children under 6 years of age should be supervised when using this product

Other information

●Store in a cool, dry place, between 15°C-30°C（59°F-86°F）

●Avoid freezing and excessive heat above 40°C（104°F）

Inactive ingredients

Aloe Barbadensis Extract, Alpha-Tocopherol, Fragrance, Glycerin,

Phenoxyethanol, Propylene Glycol, Purified Water

Package Label - Principal Display Panel

79866-012-01 75